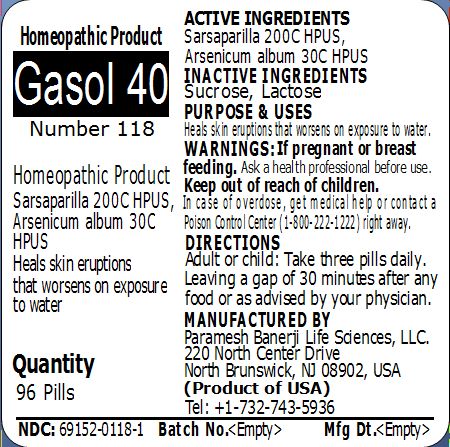 DRUG LABEL: Gasol 40 Number 118
NDC: 69152-0118 | Form: PELLET
Manufacturer: Paramesh Banerji Life Sciences LLC
Category: homeopathic | Type: HUMAN OTC DRUG LABEL
Date: 20150317

ACTIVE INGREDIENTS: SMILAX REGELII ROOT 200 [hp_C]/1 1; ARSENIC TRIOXIDE 30 [hp_C]/1 1
INACTIVE INGREDIENTS: SUCROSE; LACTOSE

Active Ingredients

Sarsaparilla 200C HPUS, Arsenicum album 30C HPUS

Inactive Ingredients

Sucrose, Lactose

Purpose

Heals skin eruptions that worsens on exposure to water

Uses

Heals skin eruptions that worsens on exposure to water

Warnings

If pregnant or breast feeding ask a health professional before use.

Keep out of reach of children. In case of overdose, get medical help or contact a Poison Control Center (1-800-222-1222) right away.

Direction

Adult or child: Take three pills daily. Leaving a gap of 30 minutes after any food or as advised by your physician.

Manufactured by

Paramesh Banerji Life Sciences, LLC

220 North Center Drive

North Brunswick, NJ 08902, USA

Product of USA

Tel: +1-732-743-5936

Principal Display Panel

Homeopathic Product

Gasol 40

Number 118

Homeopathic Product

Sarsaparilla 200C HPUS, Arsenicum album 30C HPUS

Heals skin eruptions that worsens on exposure to water

Quantity

96 Pills